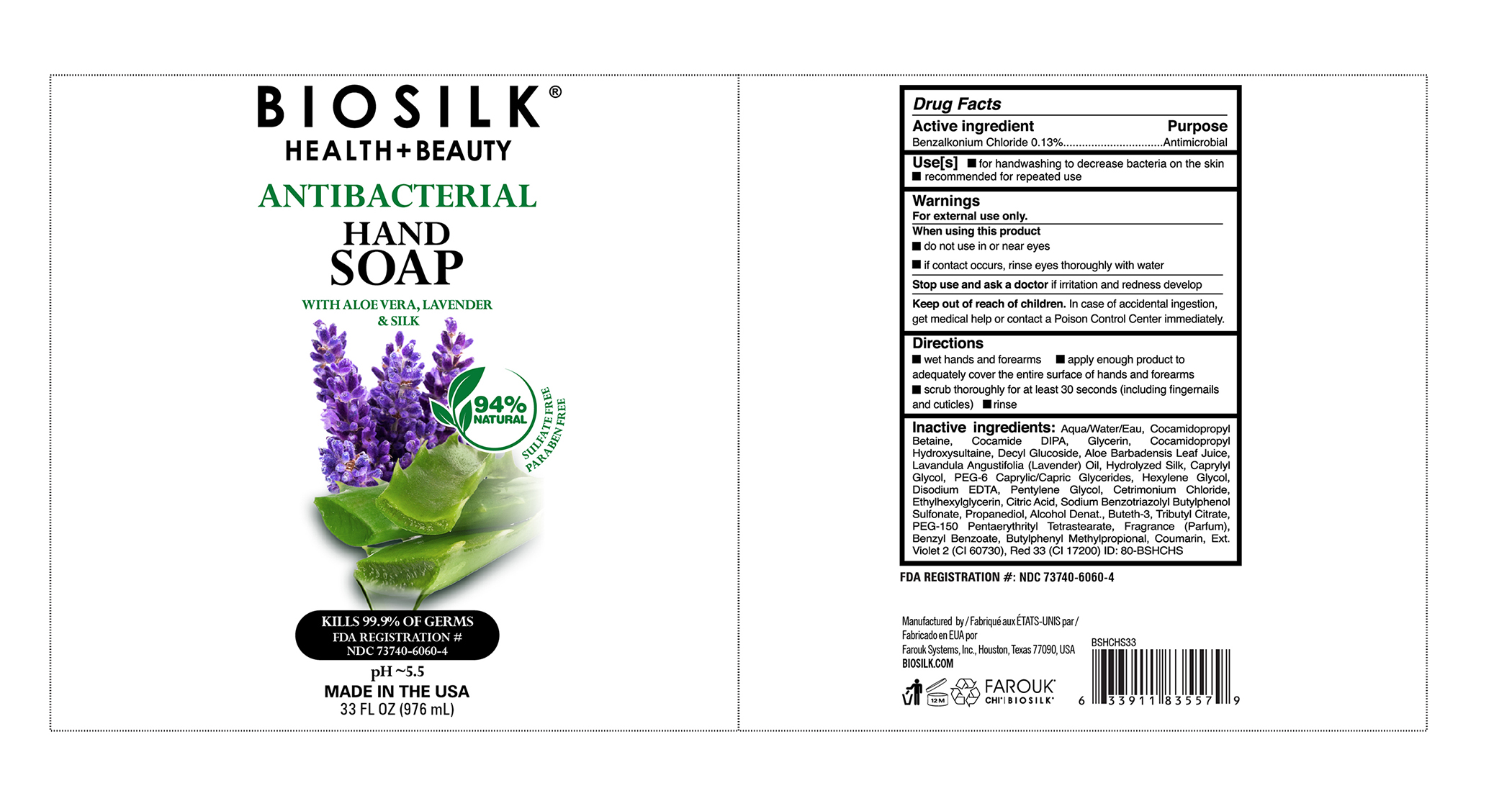 DRUG LABEL: Biosilk
NDC: 73740-6060 | Form: SOAP
Manufacturer: Farouk Systems
Category: otc | Type: HUMAN OTC DRUG LABEL
Date: 20201106

ACTIVE INGREDIENTS: BENZALKONIUM 0.13 g/100 g
INACTIVE INGREDIENTS: COCAMIDE 3.5 g/100 g; COUMARIN 0.01 g/100 g; LAVENDER OIL 0.01 g/100 g; PENTYLENE GLYCOL 0.15 g/100 g; PROPANEDIOL 0.05 g/100 g; ALCOHOL 0.011 g/100 g; CITRIC ACID MONOHYDRATE 0.1 g/100 g; SILK, ACID HYDROLYZED (1000 MW) 0.011 g/100 g; PEG-150 PENTAERYTHRITYL TETRASTEARATE 0.264 g/100 g; PEG-6 CAPRYLIC/CAPRIC GLYCERIDES 0.132 g/100 g; ALOE VERA LEAF 0.005 g/100 g; BUTYLPHENYL METHYLPROPIONAL, (+)- 0.01875 g/100 g; GLYCERIN 3 g/100 g; CAPRYLYL GLYCOL 0.5 g/100 g; CETRIMONIUM CHLORIDE 0.1 g/100 g; WATER 79.477 g/100 g; BENZYL BENZOATE 0.125 g/100 g; HEXYLENE GLYCOL 0.2 g/100 g; ETHYLHEXYLGLYCERIN 0.1 g/100 g; DECYL GLUCOSIDE 1 g/100 g; COCAMIDOPROPYL HYDROXYSULTAINE 2 g/100 g; COCAMIDOPROPYL BETAINE 9.1 g/100 g; FRAGRANCE LAVENDER & CHIA F-153480 0.09625 g/100 g

Biosilk Health + Beauty Antibacterial Hand Soap

Inactive Ingredients

Aqua/Water/Eau
Cocamidopropyl Betaine
Cocamide DIPA
Glycerin
Cocamidopropyl Hydroxysultaine
Decyl Glucoside
Aloe Barbadensis Leaf Juice
Lavandula Angustifolia (Lavender) Oil
Hydrolyzed Silk
Caprylyl Glycol
PEG-6 Caprylic/Capric Glycerides
Hexylene Glycol
Disodium EDTA
Pentylene Glycol
Cetrimonium Chloride
Ethylhexylglycerin
Citric Acid
Sodium Benzotriazolyl Butylphenol Sulfonate
Propanediol
Alcohol Denat.
Buteth-3
Tributyl Citrate
PEG-150 Pentaerythrityl Tetrastearate
Fragrance (Parfum)
Benzyl Benzoate
Butylphenyl Methylpropional
Coumarin
Ext. Violet 2 (CI 60730)
Red 33 (CI 17200)

Active Ingredient

Active Ingredient Purpose

Benzalkonium Chloride 0.13%...................Antimicrobial

Keep out of the reach of children

Keep Reach Out Of Children. In Case of accidental ingestion.get medical help or contact a Poision Control Centerimmedediatley.

Uses

Use[s] for handwashing to decrease bacteria on the skin

recomended for repeated use

Stop Use and ask a doctor

Stop Use and Ask a Doctor if irritation and redness develop

Directions

Directions

Wet hands and forearms spply enough product to adequatley cover the entire surface of hands and forearms

rub thoroughly for at least 30 seconds (including fingernails and cuticles) rinse

Uses

Use[s] for handwashing to decrease bacteria ob the skin recommended for repeated use

Warning

Warnings

Warnings

For external use only

When using this prodcut

do not use in or near eyes

if contact occurs, rinse eyes thoroughly with water

Stop use and ask a doctor if irritation and redness develop

Keep out of reach of children in case of accidental ingestion

get medical help or contact a Poison Control Center immediately

Principal Display Panel

BIOSILK ®

HEALTH + CARE

ANTIBACTERIAL

HAND

SOAP

WITH

ALOE VERA, LAVENDER & SILK

94% NATURAL

KILLS 99.9% OF GERMS

FDA REGISTRATION #

NDC 73740-6060-2

MADE IN THE USA

12 FL OZ (355) ML